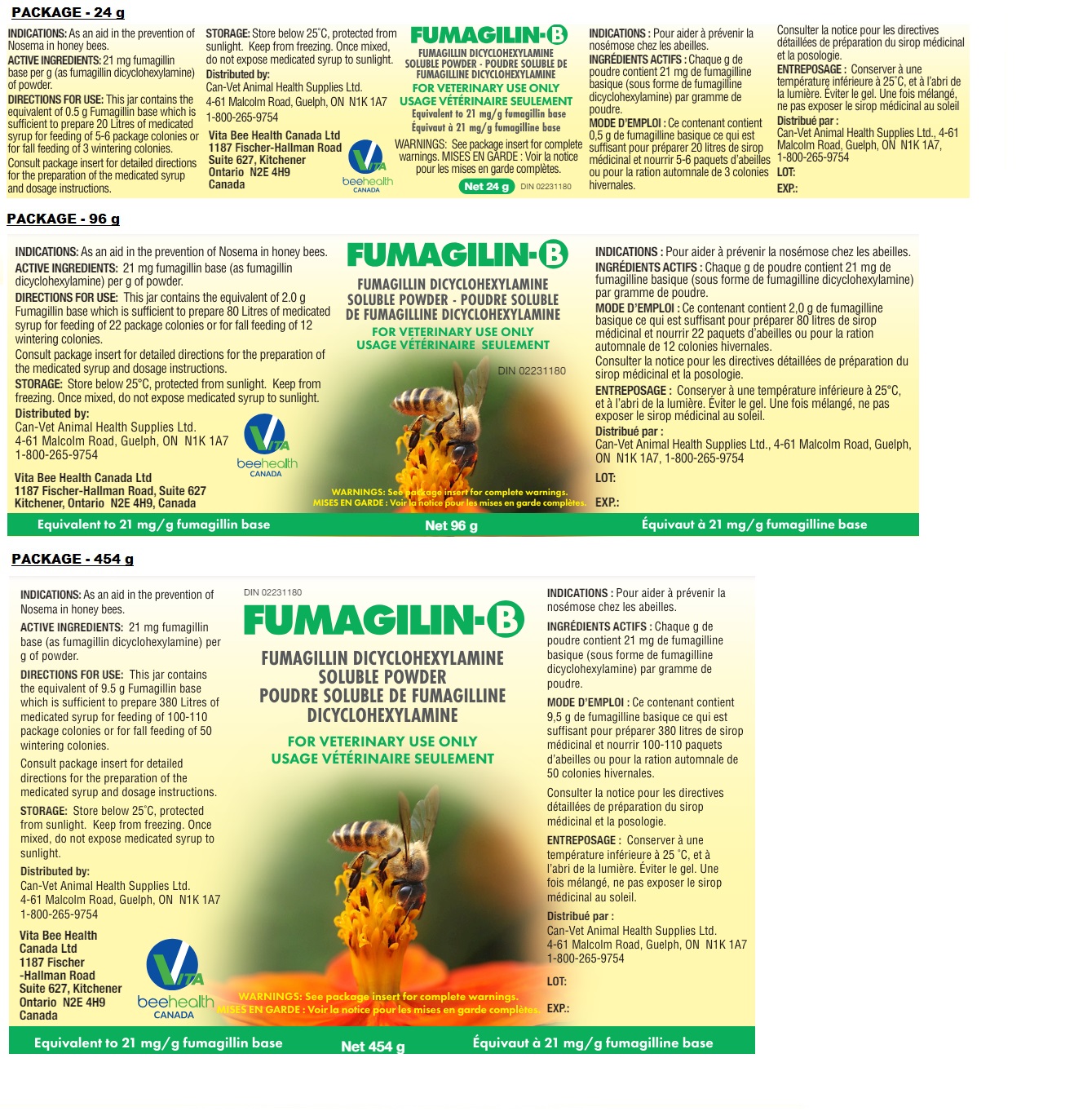 DRUG LABEL: FUMAGILIN-B
NDC: 86196-001 | Form: POWDER, FOR SOLUTION
Manufacturer: VITA BEE HEALTH CANADA LTD
Category: animal | Type: OTC ANIMAL DRUG LABEL
Date: 20240724

ACTIVE INGREDIENTS: BICYCLOHEXYLAMMONIUM FUMAGILLIN 21 mg/1 g

FUMAGILIN-B

ACTIVE INGREDIENTS:

21 mg fumagillin base (as fumagillin dicyclohexylamine) per g of powder.

INDICATIONS:

As an aid in the prevention of Nosema in honey bees.

DIRECTIONS FOR USE:

This jar contains the equivalent of 0.5 g Fumagillin base which is sufficient to prepare 20 Litres of medicated syrup for feeding of 5-6 package colonies or for fall feeding of 3 wintering colonies.

This jar contains the equivalent of 2.0 g Fumagillin base which is sufficient to prepare 80 Litres of medicated syrup for feeding of 22 package colonies or for fall feeding of 12 wintering colonies.

This jar contains the equivalent of 9.5 g Fumagillin base which is sufficient to prepare 380 Litres of medicated syrup for feeding of 100-110 package colonies or for fall feeding of 50 wintering colonies.

Consult package insert for detailed directions for the preparation of the medicated syrup and dosage instructions.

Medicated syrup is best prepared at a concentration of 25 mg Fumagillin base per Litre of syrup, usually as a 2:1 syrup (two parts of sugar to one part of water). Fumagilin-B may be dissolved in water or syrup at room temperature. For best results, heat the required amount of water to 95-122˚F, then remove the heat source and add the Fumagilin-B and the sugar in that order. To prepare this concentration of medicated syrup, use the following chart:

Mixing and Feeding Instructions in U.S. Measurements
Preparation of Medicated Syrup:

WATER | + SUGAR | = SYRUP | + FUMAGILIN-B
44 gallons | + 727 lbs. | = 100 gallons | + 16 ounces (454 g bottle)
9½ gallons | + 152 lbs. | = 21 gallons | + 3.4 ounces (96 g bottle)
2¾ gallons | + 37 lbs. | = 5.2 gallons | + 0.85 ounces (24 g bottle)
½ Gallon | + 8 lbs. | = 1 gallon | 0.18 ounces (5 g = ½ rounded tablespoon)

Good agitation is essential to assure uniform distribution of the medication.
For the protection of wintering colonies, medicated syrup is best fed in the fall if it is fed only once per year. There may be advantages to feeding medicated syrup in both the fall and the spring.
DOSAGE AND ADMINISTRATION:

Fall Feeding Medicated Syrup

2 gallons for each 2-chamber colony (approx. 30,000 bees)
1 gallon for each 1-chamber colony (approx. 18,000 bees)
3/4 gallon for each 5-frame colony (approx. 12,000 bees)
Feed additional unmedicated syrup to desired colony weight for wintering.

Spring Feeding Medicated Syrup

1 gallon for each 2-chamber colony (approx. 20,000 bees)
½ gallon for each 1-chamber colony (approx. 12,000 bees)
½ gallon for each 5-frame colony (approx. 8,000 bees)
1 gallon for each package colony.
Feed additional unmedicated syrup to provide nourishment until nectar is available.

Additional Measurements (approximate)
½ teaspoon = 1.5 g Fumagilin-B (31.5 mg activity)
1 teaspoon = 3.0 g Fumagilin-B (63 mg activity)
½ tablespoon = 5.0 g Fumagilin-B (100 mg activity)
1 tablespoon = 9.5 g Fumagilin-B (200 mg activity)
2/3 cup = 50 g Fumagilin-B (1.05 g activity)

For additional information please turn page over
Feed additional unmedicated syrup to provide nourishment until nectar is available. Package bees may have been fed medicated syrup in transit, but such feeding alone is not sufficient to protect against Nosema. Each package colony is best fed Fumagilin-B immediately after installation.
Colonies used for package production should be fed medicated syrup as a principle food source for one month prior to taking to market.
Heavily infested colonies that will no longer take in syrup may be sprayed repeatedly, directly on the bees, frame by frame with a 1:1 sugar syrup (one part sugar to one part water) containing 2 g of Fumagilin-B per Litre of syrup.

WARNINGS:

To avoid violative residues in honey, Fumagilin-B should be fed early in the spring or fall and consumed by the bees before the main honey flow begins. Complete treatments at least 4 weeks prior to the main honey flow. Honey collected in supers before the end of the 4 week withdrawal period should not be harvested for human consumption. Honey from brood nest areas of colonies treated with Fumagilin-B should not be harvested for human consumption.
When handling the product, avoid inhalation, oral exposure and direct contact with skin or eyes. Keep out of reach of children.

STORAGE:

Store below 77˚F, protected from sunlight. Keep from freezing. Once mixed, do not expose medicated syrup to sunlight.

DESCRIPTION: Fumagilin-B is a water-soluble preparation containing the antibiotic fumagillin dicyclohexylamine equivalent to 21 mg fumagillin base per gram of powder. Fumagillin base has a high specific action against Nosema apis, a microscopic single-celled parasite which causes Nosema disease in honey bees. It acts on the multiplying, disease producing parasite in the gut and is not effective against the spores. To eradicate the continuing supply of parasites, Fumagilin-B must be provided over a period of several weeks.

For additional information please turn page over

Manufactured by: Can-Vet Animal Health Supplies Ltd,
4-61 Malcolm Road, Guelph, ON N1K 1A7, Canada
Distributed in the USA by Vita Bee Health Canada Ltd.
1187 Fischer-Hallman Road, Suite 627,
Kitchener, ON N2E 4H9, Canada
Tel: +1 (519) 822-5333

FUMAGILLIN DICYCLOHEXYLAMINE SOLUBLE POWDER

FOR VETERINARY USE ONLY

WARNINGS: See package insert for complete warnings.